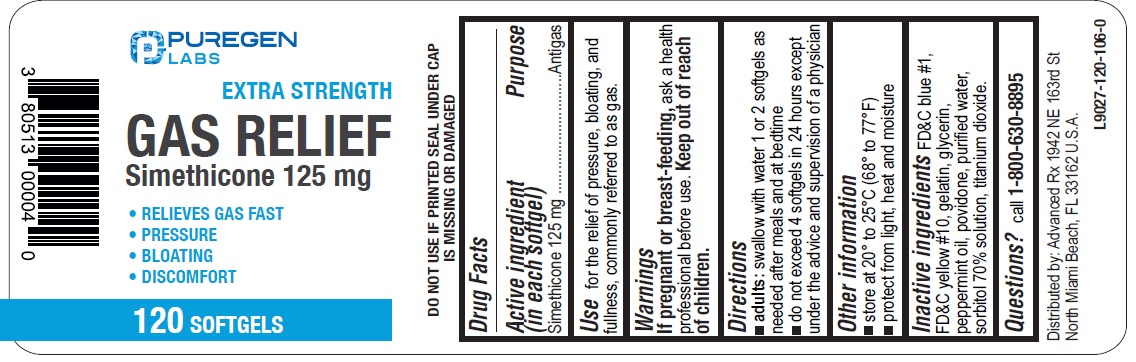 DRUG LABEL: Gas Relief
NDC: 80513-111 | Form: CAPSULE, LIQUID FILLED
Manufacturer: Advanced Rx LLC
Category: otc | Type: HUMAN OTC DRUG LABEL
Date: 20240830

ACTIVE INGREDIENTS: DIMETHICONE 125 mg/1 1
INACTIVE INGREDIENTS: FD&C BLUE NO. 1; D&C YELLOW NO. 10; GELATIN; GLYCERIN; PEPPERMINT OIL; POVIDONE, UNSPECIFIED; WATER; SORBITOL; TITANIUM DIOXIDE

Active ingredient (in each softgel)

Simethicone 125 mg

Purpose

Antigas

Use

for the relief of pressure, bloating, and fullness, commonly referred to as gas.

KEEP OUT OF REACH OF CHILDREN

If pregnant or breast-feeding,ask a health professional before use.

Keep out of reach of children.

Directions

- adults:swallow with water 1 or 2 softgels as needed after meals and at bedtime
- do not exceed 4 softgels in 24 hours except under the advice and supervision of a physician

Other information

- store at 20° to 25°C (68° to 77°F)
- protect from light, heat and moisture
- DO NOT USE IF PRINTED SEAL UNDER CAP IS MISSING OR DAMAGED

Inactive ingredients

FD&C blue #1, FD&C yellow #10, gelatin, glycerin, peppermint oil, povidone, purified water, sorbitol 70% solution, titanium dioxide.

Questions?

call 1-800-630-8895

Distributed by:

Advanced Rx LLC

1942 NE 163rd St North Miami Beach,

FL 33162 U.S.A.

PACKAGE LABEL

NDC 80513-111-12

EXTRA STRENGTH

GAS RELIEF

Simethicone 125 mg

• RELIEVES GAS FAST

• PRESSURE

• BLOATING

• DISCOMFORT

120 SOFTGELS